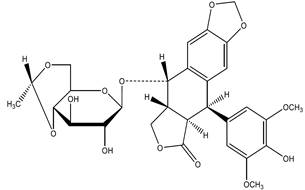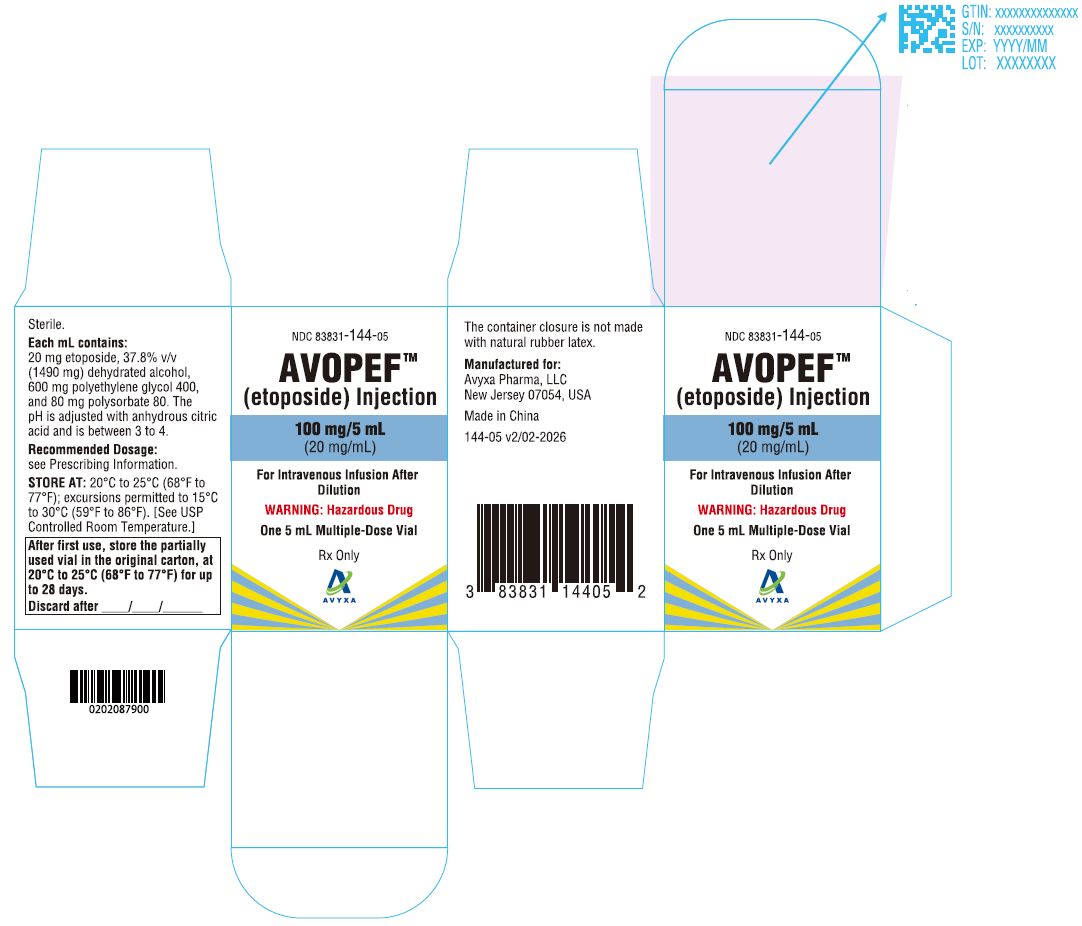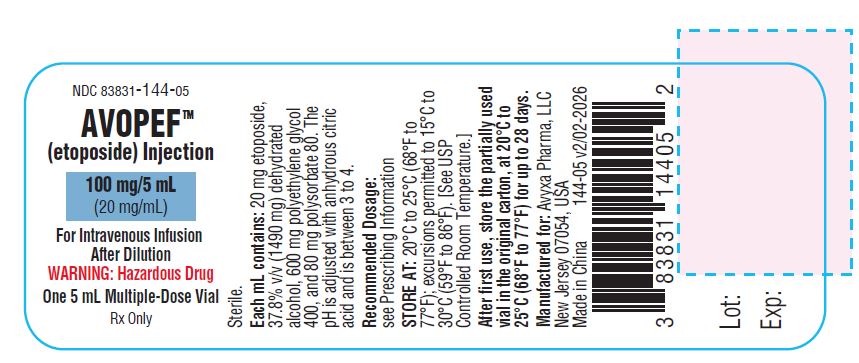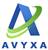 DRUG LABEL: Avopef
NDC: 83831-144 | Form: INJECTION
Manufacturer: Avyxa Pharma, LLC
Category: prescription | Type: HUMAN PRESCRIPTION DRUG LABEL
Date: 20260216

ACTIVE INGREDIENTS: ETOPOSIDE 100 mg/5 mL
INACTIVE INGREDIENTS: ANHYDROUS CITRIC ACID; POLYSORBATE 80; POLYETHYLENE GLYCOL 400; DEHYDRATED ALCOHOL

HIGHLIGHTS OF PRESCRIBING INFORMATION

These highlights do not include all the information needed to use AVOPEF safely and effectively. See full prescribing information for AVOPEF.
AVOPEFTM (etoposide) injection, for intravenous use
Initial U.S. Approval: 1983

WARNING: SEVERE MYELOSUPPRESSION

See full prescribing information for complete boxed warning.

- AVOPEF can cause severe myelosuppression resulting in infection or bleeding. (5.1)
- Do not administer AVOPEF to patients with absolute neutrophil counts of less than 500 cells/mm^3or platelets less than 50,000 cells/mm^3. (5.1)
- Monitor complete blood cell counts, prior to the administration of AVOPEF and before each subsequent cycle, and at appropriate intervals during and after therapy. (5.1)

1 INDICATIONS AND USAGE

AVOPEF is a topoisomerase inhibitor indicated, in combination with other chemotherapy and/or immunotherapy, for the treatment of adult patients with:

- Refractory testicular cancer (1.1)
- Small cell lung cancer (1.2)

2 DOSAGE AND ADMINISTRATION

- Refractory Testicular Cancer: 50 mg/m^2 to 100 mg/m^2 administered intravenously daily on Days 1 to 5, or 100 mg/m^2 administered intravenously daily on Days 1, 3 and 5. (2.2)
- Small Cell Lung Cancer: 35 mg/m^2 administered intravenously daily on days 1 to 4, or 50 mg/m^2 administered intravenously daily on days 1 to 5. (2.3)
- Dilute AVOPEF prior to intravenous infusion over 30- to 60-minutes. (2.5)

3 DOSAGE FORMS AND STRENGTHS

- Injection: 100 mg/5 mL (20 mg/mL) in a multiple-dose vial. (3)

4 CONTRAINDICATIONS

Hypersensitivity to etoposide or any of its excipients. (4)

5 WARNINGS AND PRECAUTIONS

- Severe Myelosuppression: Monitor complete blood counts before each AVOPEF administration and at appropriate intervals during and after therapy. Interrupt AVOPEF for absolute neutrophil counts below 500 cells/mm^3or platelet counts below 50,000 cells/mm^3. (5.1)
- Hypersensitivity and Infusion-Related Reactions: At the first sign of hypersensitivity, stop the infusion and administer volume expanders, corticosteroids, antihistamines, and pressor agents as appropriate. Permanently discontinue AVOPEF in patients who experience a severe hypersensitivity reaction. Hypotension has occurred after rapid intravenous injection. (5.2)
- Extravasation Resulting in Tissue Necrosis: Extravasation of etoposide can result in swelling, pain, cellulitis, and tissue necrosis. (5.3)
- Secondary Leukemia: Secondary leukemia has occurred with use of etoposide. (5.4)
- Risk of Increased AVOPEF Toxicity with Low Serum Albumin: Monitor serum albumin during treatment with AVOPEF. Patients with low serum albumin may have increased concentrations of unbound etoposide and may be at an increased risk for etoposide associated adverse reactions. (5.5)
- Alcohol Content: The alcohol content in a dose of AVOPEF may affect the central nervous system. This may include impairment of a patient's ability to drive or use machines immediately after infusion. (5.6)
- Embryo-Fetal Toxicity: AVOPEF can cause fetal harm. Advise patients of the potential risk to a fetus and to use effective contraception. (5.7)

6 ADVERSE REACTIONS

The most common adverse reactions are, myelosuppression, hypersensitivity, nausea/vomiting, and alopecia. (6.1)

To report SUSPECTED ADVERSE REACTIONS, contact Avyxa Pharma, LLC at 1-888-520-0954 or FDA at 1-800-FDA-1088 or www.fda.gov/medwatch.

7 DRUG INTERACTIONS

- CYP3A Inhibitors and CYP3A Inducers: Avoid concomitant use of strong CYP3A inhibitors and strong CYP3A inducers with AVOPEF. (7.1)
- Vitamin K Antagonists: Monitor INR more frequently and modify the dosage of the vitamin K antagonists as appropriate. Co-administration of AVOEPF with warfarin can result in elevated international normalized ratio (INR). (7.2)

8 USE IN SPECIFIC POPULATIONS

- Lactation: Advise not to breastfeed. (8.2)
- Renal Impairment: Reduce the recommended dose for patients with creatinine clearance of 15 to 50 mL/min. (2.4)

FULL PRESCRIBING INFORMATION

WARNING: SEVERE MYELOSUPPRESSION

- AVOPEF can cause severe myelosuppression resulting in infection or bleeding [see Warnings and Precautions (5.1)].
- Do not administer AVOPEF to patients with absolute neutrophil counts of less than 500 cells/mm^3or platelets less than 50,000 cells/mm^3 [see Warnings and Precautions (5.1)].
- Monitor complete blood cell counts, prior to the administration of AVOPEF and before each subsequent cycle, and at appropriate intervals during and after therapy [see Warnings and Precautions (5.1)].

1 INDICATIONS AND USAGE

1.1 Refractory Testicular Cancer

AVOPEF, in combination with chemotherapy, is indicated for the treatment of refractory testicular cancer in adult patients.

1.2 Small Cell Lung Cancer

AVOPEF, in combination with chemotherapy and immunotherapy, is indicated for the first-line treatment of small cell lung cancer (SCLC) in adult patients.

2 DOSAGE AND ADMINISTRATION

2.1 Important Dosage and Administration Information

- Dilute AVOPEF to a final concentration of 0.2 to 0.4 mg/mL prior to administration [see Dosage and Administration (2.5)].
- Administer diluted AVOPEF by intravenous infusion over 30 to 60 minutes to reduce the risk of infusion-related reactions including hypotension [see Dosage and Administration (2.5)].
- Before each AVOPEF administration and at appropriate intervals during and after therapy, monitor complete blood counts with differential and serum albumin [see Warnings and Precautions (5.1,5.5)].
- If severe reactions occur, reduce the dosage or discontinue AVOPEF and take appropriate corrective measures according to the clinical judgment of the healthcare provider.

2.2 Recommended Dosage for Refractory Testicular Cancer

The recommended dosage of AVOPEF is:

- 50 mg/m^2 to 100 mg/m^2 administered intravenously daily on Days 1 to 5, or
- 100 mg/m^2 administered intravenously daily on Days 1, 3 and 5

Repeat treatment cycles every 3 to 4 weeks.

2.3 Recommended Dosage for Small Cell Lung Cancer

The recommended dosage of AVOPEF is:

- 35 mg/m^2 administered intravenously daily on Days 1 to 4, or
- 50 mg/m^2administered intravenously daily on Days 1 to 5

Repeat treatment cycles every 3 to 4 weeks.

2.4 Recommended Dosage in Patients with Renal Impairment

No dosage modification is recommended for patients with creatinine clearance (CLcr) > 50 mL/min. The recommended dosage of AVOPEF in patients with CLcr of 15 to 50 mL/min is listed in Table 1.

Table 1: Recommended Dosage of AVOPEF in Patients with Creatine Clearance of 15 to 50 mL/min
 | Recommended AVOPEF Dosage*
Refractory Testicular Cancer | 37 mg/m^2 to 75 mg/m^2 Days 1 through 5
Refractory Testicular Cancer | 75 mg/m^2 Days 1, 3 and 5
Small Cell Lung Cancer | 26 mg/m^2 Days 1 through 4
Small Cell Lung Cancer | 37 mg/m^2 Days 1 through 5
*Repeat treatment cycles every 3 to 4 weeks.

A recommended dosage of AVOPEF has not been established for patients with creatinine clearance < 15 mL/min.

2.5 Preparation for Intravenous Administration

Preparation

- AVOPEF is a hazardous drug. Follow applicable special handling and disposal procedures. [see References (15)].
- Dilute AVOPEF with either 5% Dextrose Injection, USP, or 0.9% Sodium Chloride Injection, USP, to a final concentration of 0.2 to 0.4 mg/mL. If solutions of AVOPEF are prepared at concentrations above 0.4 mg/mL, precipitation may occur.
- Parenteral drug products should be inspected visually for particulate matter and discoloration prior to administration, whenever solution and container permit.

Administration

- Do not administer AVOPEF by rapid intravenous injection. To reduce the risk of infusion-related reactions including hypotension, administer diluted AVOPEF intravenously over 30 to 60 minutes. A longer duration of administration may be used if there is a large volume of fluid to be infused.

Storage

- AVOPEF, diluted to a concentration of 0.2 mg/mL is stable for 96 hours or diluted to a concentration of 0.4 mg/mL is stable for 24 hours at room temperature (25°C) under normal room fluorescent light in polyvinyl chloride (PVC) container.
- After first use, store the partially used multiple-dose vial in the original carton at controlled room temperature, 20°C to 25° C (68°F to 77° F) for up to 28 days. Discard unused portion of the multiple-dose vial after 28 days.

3 DOSAGE FORMS AND STRENGTHS

Injection: 100 mg/5 mL (20 mg/mL) of etoposide as a sterile, clear, colorless to light yellow liquid in a multiple-dose vial.

4 CONTRAINDICATIONS

AVOPEF is contraindicated in patients with hypersensitivity to etoposide or any of its excipients.

5 WARNINGS AND PRECAUTIONS

5.1 Severe Myelosuppression

AVOPEF can cause severe and fatal myelosuppression, including neutropenia, febrile neutropenia, anemia, and thrombocytopenia.

Monitor complete blood counts with differential before each AVOPEF administration and at appropriate intervals during and after treatment with AVOPEF. Do not administer AVOPEF to patients with absolute neutrophil counts of less than 500 cells/mm^3or platelets less than 50,000 cells/mm^3.

5.2 Hypersensitivity and Infusion-Related Reactions

AVOPEF can cause severe and fatal infusion-related reactions including anaphylactic reactions characterized by chills, fever, tachycardia, bronchospasm, dyspnea and hypotension [see Adverse Reactions (6.1)]. Hypertension and flushing have occurred.

At the first sign of hypersensitivity, stop the infusion and administer volume expanders, corticosteroids, antihistamines, and pressor agents as appropriate. Permanently discontinue AVOPEF in patients who experience a severe hypersensitivity reaction. Hypotension due to rapid intravenous injection has also occurred. To reduce the risk of hypotension due to an infusion-related reaction, administer AVOPEF by intravenous infusion over 30 to 60 minutes [see Dosage and Administration (2.5)].

5.3 Extravasation Resulting in Tissue Necrosis

Extravasation of etoposide can result in swelling, pain, cellulitis, and tissue necrosis.

5.4 Secondary Leukemia

Secondary leukemia has occurred with use of etoposide.

5.5 Risk of Increased AVOPEF Toxicity with Low Serum Albumin

Etoposide is highly protein-bound. Patients with low serum albumin may have increased concentrations of unbound etoposide and may be at an increased risk for etoposide associated adverse reactions. Monitor for increased adverse reactions during treatment with AVOPEF in patients with low serum albumin.

5.6 Alcohol Content

The alcohol content in a dose of AVOPEF may affect the central nervous system and should be taken into account for patients in whom alcohol intake should be avoided or minimized. Consideration should be given to the alcohol content in AVOPEF on the ability to drive or use machines immediately after the infusion. Each administration of AVOPEF at 100 mg/m^2 delivers 1.5 g/m^2 of ethanol. For a patient with a BSA of 2.0 m^2 this would deliver 3.0 grams of ethanol [see Description (11)]. Other etoposide products may have a different amount of alcohol or no alcohol.

5.7 Embryo-Fetal Toxicity

Based on findings from animal studies and its mechanism of action, AVOPEF can cause fetal harm when administered to a pregnant woman. In animal reproduction studies, intravenous or intraperitoneal administration of etoposide to pregnant animals during the period of organogenesis caused embryo-fetal mortality and structural abnormalities at doses below the recommended human dose of 50 mg/m^2 based on body surface area (BSA).

Advise pregnant women and females of reproductive potential of the potential risk to a fetus. Advise female patients of reproductive potential to use effective contraception during treatment with AVOPEF and for 6 months after the last dose. Advise males with female partners of reproductive potential to use effective contraception during treatment with AVOPEF and for 4 months after the last dose [see Use in Specific Populations (8.1, 8.3)].

6 ADVERSE REACTIONS

The following clinically significant adverse reactions are discussed in more detail in other sections of the labeling.

- Severe Myelosuppression [see Warnings and Precautions (5.1)]
- Hypersensitivity and Infusion-Related Reactions [see Warnings and Precautions (5.2)]
- Extravasation Resulting in Tissue Necrosis [see Warnings and Precautions (5.3)]
- Secondary Leukemia [see Warnings and Precautions (5.4)]
- Risk of Increased AVOPEF Toxicity with Low Serum Albumin [see Warnings and Precautions (5.5)]
- Alcohol Content [see Warnings and Precautions (5.6)]

6.1 Clinical Trials Experience

Because clinical trials are conducted under widely varying conditions, adverse reaction rates observed in the clinical trials of a drug cannot be directly compared to rates in the clinical trials of another drug and may not reflect the rates observed in clinical practice.

Blood and lymphatic system disorders: acute leukemia, myelosuppression

Eye disorders: transient cortical blindness

Gastrointestinal disorders: abdominal pain, anorexia, constipation, diarrhea, dysgeusia, dysphagia, esophagitis, mucositis, nausea, stomatitis and vomiting

General disorders and administration site conditions: fatigue, fever, and infusion site extravasation with necrosis

Hepatobiliary disorders: hepatoxicity, metabolic acidosis

Immune system disorders: allergic reaction, anaphylactic reaction (including chills, fever, tachycardia, bronchospasm, dyspnea, hypotension, hypertension, flushing, facial swelling, tongue swelling, coughing, diaphoresis, cyanosis, tightness in throat, laryngospasm, back pain, loss of consciousness, hypersensitivity-associated apnea), hypersensitivity, infusion-related reaction.

Infections: febrile neutropenia

Nervous system disorders: optic neuritis, peripheral neuropathy and seizure

Respiratory, thoracic and mediastinal disorders: interstitial pneumonitis and pulmonary fibrosis

Skin and subcutaneous tissue disorders: alopecia, pigmentation changes (including pigmented bands in nails, skin darkening and discoloration of tongue and teeth), pruritic erythematous maculopapular rash, pruritus, radiation recall dermatitis, rash, Stevens-Johnson syndrome (SJS), toxic epidermal necrolysis (TEN) and urticaria

Vascular disorders: hypotension following rapid intravenous administration [see Dosage and Administration (2.5)], perivasculitis

7 DRUG INTERACTIONS

7.1 Effect of Other Drugs on AVOPEF

CYP3A Inhibitors

Avoid concomitant use of strong CYP3A inhibitors.

Etoposide is a CYP3A4 substrate. Strong CYP3A inhibitors may increase etoposide exposure, which may increase the risk of AVOPEF-associated adverse reactions [see Clinical Pharmacology (12.3)].

CYP3A Inducers

Avoid concomitant use of strong CYP3A inducers.

Etoposide is a CYP3A4 substrate. Strong CYP3A inducers may reduce etoposide exposure, which may decrease the effectiveness of AVOPEF [see Clinical Pharmacology (12.3)].

7.2 Effect of AVOPEF on Other Drugs

Vitamin K Antagonists

Monitor INR more frequently and modify the dosage of the vitamin K antagonists as appropriate.

Co-administration of AVOEPF with warfarin can result in elevated international normalized ratio (INR).

8 USE IN SPECIFIC POPULATIONS

8.1 Pregnancy

Risk Summary

Based on findings in animal studies and its mechanism of action [see Clinical Pharmacology (12.1)], AVOPEF can cause fetal harm when administered to a pregnant woman. There are no available data on the use of AVOPEF in pregnant women to inform a drug-associated risk. AVOPEF contains alcohol which can interfere with neurobehavioral development [see Clinical Considerations]. In animal reproduction studies, intravenous or intraperitoneal administration of etoposide to pregnant animals during the period of organogenesis caused embryo-fetal mortality and structural abnormalities at doses below the recommended human dose of 50 mg/m^2 based on body surface area (BSA). Advise pregnant women and females of reproductive potential of the potential risk to a fetus. Advise female patients of reproductive potential to use effective contraception during treatment with AVOPEF and for 6 months after the last dose [see Use in Specific Populations (8.1, 8.3) and Clinical Pharmacology (12.1)]. In the U.S. general population, the estimated background risk of major birth defects and miscarriage in clinically recognized pregnancies is 2% to 4% and of miscarriage is 15% to 20%, respectively.

Clinical Considerations

AVOPEF contains alcohol [see Warnings and Precautions (5.6)]. Published studies have demonstrated that alcohol is associated with fetal harm including central nervous system abnormalities, behavioral disorders, and impaired intellectual development.

Data

Animal Data

In rats, an intravenous etoposide dose of 0.4 mg/kg/day (approximately 0.05 times the human dose of 50 mg/m^2 based on BSA) during organogenesis caused maternal toxicity, embryotoxicity, and teratogenicity (skeletal abnormalities, exencephaly, encephalocele, and anophthalmia); higher doses of 1.2 and 3.6 mg/kg/day (approximately 0.14- and 0.5-times the human dose of 50 mg/m^2 based on BSA) resulted in 90% and 100% embryonic resorptions, respectively. In mice, a single etoposide dose of 1.0 mg/kg (approximately 0.06 times the human dose of 50 mg/m^2 based on BSA) administered intraperitoneally on Days 6, 7, or 8 of gestation caused embryotoxicity, cranial abnormalities, and major skeletal malformations. An intraperitoneal dose of 1.5 mg/kg (approximately 0.10-times the human dose 50 mg/m^2 based on BSA) on Day 7 of gestation caused an increase in the incidence of intrauterine death, fetal malformations, and a significant decrease in the average fetal body weight.

8.2 Lactation

Risk Summary

There is no information regarding the presence of etoposide or its metabolites in human milk or the effects on a breastfed child or on milk production. Because the potential for serious adverse reactions in breastfed children, advise women not to breastfeed during treatment with AVOPEF and for 1 week after the last dose.

8.3 Females and Males of Reproductive Potential

Based on animal data and its mechanism of action, AVOPEF can cause fetal harm when administered to pregnant women [see Use in Specific Population (8.1)].

Pregnancy Testing

Verify the pregnancy status of female patients of reproductive potential prior to initiating AVOPEF.

Contraception

Females

Advise females of reproductive potential to use effective contraception during treatment with AVOPEF and for 6 months after the last dose [see Use in Specific Populations (8.1) and Nonclinical Toxicology (13.1)].

Males

Due to the potential for genotoxicity, advise males with female partners of reproductive potential to use effective contraception during treatment with AVOPEF and for 4 months after the last dose [see Nonclinical Toxicology (13.1)].

Infertility

Females

In females of reproductive potential, AVOPEF may cause infertility and result in amenorrhea. Premature menopause can occur with AVOPEF. Recovery of menses and ovulation is related to age at treatment.

Males

In male patients, AVOPEF may result in oligospermia, azoospermia, and permanent loss of fertility. Sperm counts have been reported to return to normal levels in some men, and in some cases, have occurred several years after the end of therapy [See Nonclinical Toxicology (13.1)].

8.4 Pediatric Use

The safety and effectiveness of AVOPEF have not been established in pediatric patients.

8.5 Geriatric Use

Clinical studies of etoposide for the treatment of refractory testicular tumors did not include sufficient numbers of patients aged 65 years and older to determine whether they respond differently from younger patients. Other reported clinical experience demonstrated that patients 65 years and older experienced more myelosuppression, anorexia, mucositis, dehydration, somnolence, elevated blood urea nitrogen (BUN), infectious complications and alopecia compared to younger patients.

In general, dosage selection for an older patient should be cautious, usually starting at the low end of the dosing range, reflecting the greater frequency of decreased hepatic, renal, or cardiac function, and of concomitant disease or other drug therapy.

8.6 Renal Impairment

Reduce the dose of AVOPEF in patients with creatinine clearance (CLcr) of 15 to 50 mL/min [see Dosage and Administration (2.4)]. No dosage modification is recommended for patients with CLcr > 50 mL/min.

11 DESCRIPTION

AVOPEF injection contains etoposide, a topoisomerase inhibitor. The chemical name for etoposide is 4'-Demethylepipodophyllotoxin 9-[4,6-O-(R)-ethylidene-β-D glucopyranoside] and has the following structural formula:

Etoposide is a white or off-white crystalline powder with the molecular formula C29H32O13 and a molecular weight of 588.56. It is sparingly soluble in acetone, slightly soluble in methanol or in chloroform, very slightly soluble in ethanol and practically insoluble in water.

AVOPEF (etoposide) Injection is a sterile, clear, colorless to light yellow liquid available in 100 mg/5 mL multiple-dose vials containing 20 mg/mL of etoposide for intravenous administration. Each mL contains 20 mg etoposide, 37.8% v/v (1490 mg) dehydrated alcohol, 600 mg polyethylene glycol 400, and 80 mg polysorbate 80. The pH is adjusted with anhydrous citric acid and is between 3 to 4. Vial headspace contains nitrogen.

12 CLINICAL PHARMACOLOGY

12.1 Mechanism of Action

Etoposide causes the induction of DNA strand breaks by an interaction with DNA-topoisomerase II or the formation of free radicals, leading to cell cycle arrest, primarily at the G2 stage of the cell cycle, and cell death.

12.2 Pharmacodynamics

Etoposide exposure-response relationships and the time course of pharmacodynamic response are unknown.

12.3 Pharmacokinetics

Etoposide total systemic exposure (AUC) and the maximum plasma concentration (Cmax) increases in dose proportional manner over dosage range of 100 to 600 mg/m^2 (6 times the maximum approved recommended dose). Etoposide does not accumulate following daily administration of 100 mg/m^2 for 4 to 5 days.

Distribution

Etoposide mean volume of distribution at steady state is 7 L/m^2 to 17 L/m^2.

No clinically significant amount of etoposide distributes into the CSF.

Etoposide plasma protein binding is 97% in vitro (primarily albumin).

Elimination

Etoposide elimination half-life is 4 hours to 11 hours. Total body clearance is 16 mL/min/m^2 to 36 mL/min/m^2 over a range of 100 mg/m^2 to 600 mg/m^2 (6 times the maximum approved recommended dose). The mean renal clearance of etoposide is 7 mL/min/m^2 to 10 mL/min/m^2 over a dose range of 80 mg/m^2 to 600 mg/m^2 (6 times the maximum approved recommended dose).

Metabolism

Etoposide is metabolized by opening of the lactone ring, O-demethylation and conjugation (i.e., glucuronidation and sulfation. O-demethylation occurs through CY3A to the active catechol metabolite.

Excretion

After intravenous administration of ^14C-etoposide [100 to 124 mg/m^2 (1.2 times the maximum approved recommended dose)], mean recovery of radioactivity in the urine was 56% of the dose at 120 hours, 45% of which was excreted as etoposide; fecal recovery of radioactivity was 44% of the dose at 120 hours.

Specific Populations

No clinically significant differences in pharmacokinetic parameters of etoposide were observed based on age and sex.

Patients with Renal Impairment

Patients with impaired renal function have exhibited reduced total body clearance, increased AUC, and a lower volume of distribution at steady state.

Drug Interactions

In vitro studies

Phenylbutazone, sodium salicylate, and aspirin displaced protein-bound etoposide in vitro.

13 NONCLINICAL TOXICOLOGY

13.1 Carcinogenesis, Mutagenesis, Impairment of Fertility

Carcinogenesis

A single intravenous dose of etoposide at ≥ 4 times the human dose of 50 mg/m^2 based on BSA caused benign and malignant breast tumors in female rats and mice.

Mutagenesis

Etoposide was mutagenic in an in vitro bacterial reverse mutation (Ames) assay.

Impairment of Fertility

Irreversible testicular atrophy was present in rats treated with etoposide intravenously for 30 days at 0.5 mg/kg/day (approximately 0.06 times the human dose of 50 mg/m^2 based on BSA).

A single intravenous dose of etoposide at approximately 5 times the human dose of 50 mg/m^2 based on BSA caused accelerated atrophic processes in the ovaries of rats, 3 months post-treatment. In vitro, etoposide treatment resulted in damage of pre-follicular fetal ovaries.

15 REFERENCES

1. OSHA Hazardous Drugs. OSHA. http://www.osha.gov/SLTC/hazardousdrugs/index.html

16 HOW SUPPLIED/STORAGE AND HANDLING

AVOPEF (etoposide) Injection, 100 mg/5 mL (20 mg/mL) is a sterile, clear, colorless to light yellow liquid available in multiple-dose glass vials as follows:

NDC Number | Strength | Package
83831-144-05 | 100 mg/5 mL (20 mg/mL) | 1 multiple-dose vial in 1 carton.

This container closure is not made with natural rubber latex.

Storage and Handling

Store at 20°C to 25° C (68°F to 77° F); excursions permitted to 15°C to 30°C (59°F to 86°F). [See USP Controlled Room Temperature]. After first use, store the partially used multiple-dose vial in the original carton at controlled room temperature, 20°C to 25°C (68°F to 77°F) for up to 28 days [see Dosage and Administration (2.5)].

AVOPEF is a hazardous drug. Follow applicable special handling and disposal procedures [see References (15)].

17 PATIENT COUNSELING INFORMATION

Severe Myelosuppression

Inform patients that AVOPEF can cause severe myelosuppression. Advise patients that periodic monitoring of their blood counts is required during treatment with AVOPEF. Advise patients to contact their healthcare provider for any signs or symptoms of myelosuppression [see Warnings and Precautions (5.1)].

Hypersensitivity and Infusion-Related Reactions

Inform patients that AVOPEF can cause severe infusion-related reactions, allergic reactions and anaphylaxis. Advise patients to immediately call their healthcare provider to report any signs or symptoms of an infusion-related reaction, allergic reaction or anaphylaxis [see Warnings and Precautions (5.2)].

Risk of Increased AVOPEF Toxicity with Low Serum Albumin

Inform patients that the risk of AVOPEF toxicity is increased with low serum albumin. Advise patients that periodic monitoring of their serum albumin is required during treatment with AVOPEF. Advise patients to contact their healthcare provider if they experience signs or symptoms of low serum albumin or AVOPEF toxicity [see Warnings and Precautions (5.5)].

Secondary Leukemia

Inform patients that AVOPEF can cause secondary leukemia. Advise patients that periodic monitoring is recommended during and after treatment with AVOPEF and to contact their healthcare provider if they experience signs or symptoms of leukemia [see Warnings and Precautions (5.4)].

Alcohol Content

Advise patients of the effects of alcohol in AVOPEF, including possible effects on the central nervous system. Advise patients in whom alcohol should be avoided or minimized to consider the alcohol content of AVOPEF. AVOPEF at 100 mg/m^2 delivers 1.5 g/m^2 of ethanol. For a patient with a BSA of 2.0 m^2 this delivers 3.0 grams of ethanol [see Description (11)]. Alcohol impairs the ability to drive or use machines [see Warnings and Precautions (5.6)].

Embryo-Fetal Toxicity

- Advise pregnant women and females of reproductive potential of the potential risk to a fetus and to inform their healthcare provider with a known or suspected pregnancy [see Warnings and Precautions (5.7) and Use in Specific Populations (8.1)].
- Advise females of reproductive potential to use effective contraception during treatment with AVOPEF and for 6 months after the last dose [see Use in Specific Populations (8.3)].
- Advise males with female partners of reproductive potential to use effective contraception during treatment with AVOPEF and for 4 months after the last dose [see Nonclinical Toxicology (13.1)].

Lactation

Advise women not to breastfeed during treatment with AVOPEF and for 1 week after the last dose [see Use in Specific Populations (8.2)].

Infertility

Advise males and females of reproductive potential that AVOPEF may impair fertility [see Use in Specific Populations (8.3) and Nonclinical Toxicology (13.1)].

Manufactured for:

Avyxa Pharma, LLC

New Jersey 07054, USA

Made in China

PACKAGE LABEL.PRINCIPAL DISPLAY PANEL

Avopef-carton- 20mg/mL
Avopef-vial- 20mg/mL